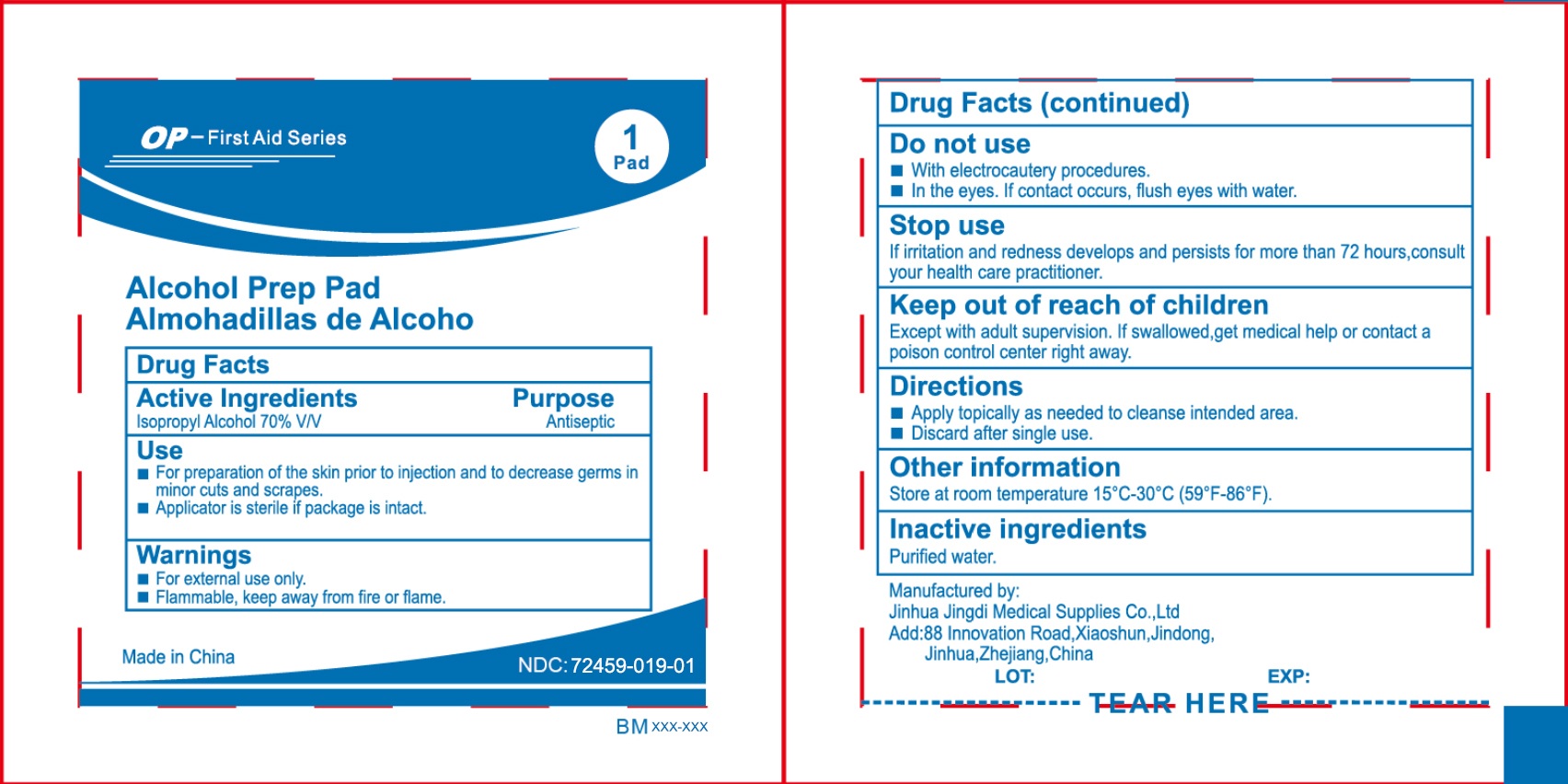 DRUG LABEL: OP-First Aid Series ALCOHOL PREP PADS STERILE
NDC: 72459-019 | Form: CLOTH
Manufacturer: Yiwu Ori-Power Medtech Co.,Ltd.
Category: otc | Type: HUMAN OTC DRUG LABEL
Date: 20250822

ACTIVE INGREDIENTS: ISOPROPYL ALCOHOL 70 mL/100 mL
INACTIVE INGREDIENTS: WATER 30 mL/100 mL

OP-First Aid Series Alcohol Prep Pad

ACTIVE INGREDIENT

Isopropyl Alcohol, 70% v/v

DESCRIPTION

Use for preparation of skin prior to injection

INACTIVE INGREDIENT

Purified Water

WARNINGS

For external use only. Flammable, keep away from fire or flame.

Do not use

- with electrocautery procedures
- in the eyes
- on mucous membranes
- on irritated skin.

Stop use and ask a doctor if

irritation or redness develops.

Keep out of reach of children.

If swallowed, get medical help or contact a Poison Control center right away.

DOSAGE AND ADMINISTRATION

Apply topically as needed to cleanse intendend area；

Apply the product to the skin, take the injection or puncture site as the center, slowly rotate from the inside to the outside, and gradually apply the product for two times, the disinfection area should be more than 5cmx5cm, and the action time should be 1min.

INDICATIONS AND USAGE

Use for preparation of skin prior to injection，apply the product to the skin, take the injection or puncture site as the center, slowly rotate from the inside to the outside, and gradually apply the product for two times, the disinfection area should be more than 5cmx5cm, and the action time should be1min.Please clean before disinfection.

PURPOSE

Use for preparation of skin prior to injection, to clean the skin.

keep out of reach of children.

Do not use the product when its packaging is damaged.

OTHER SAFETY INFORMATION

Store at room temperature 15 - 30°C (59 - 86°F)